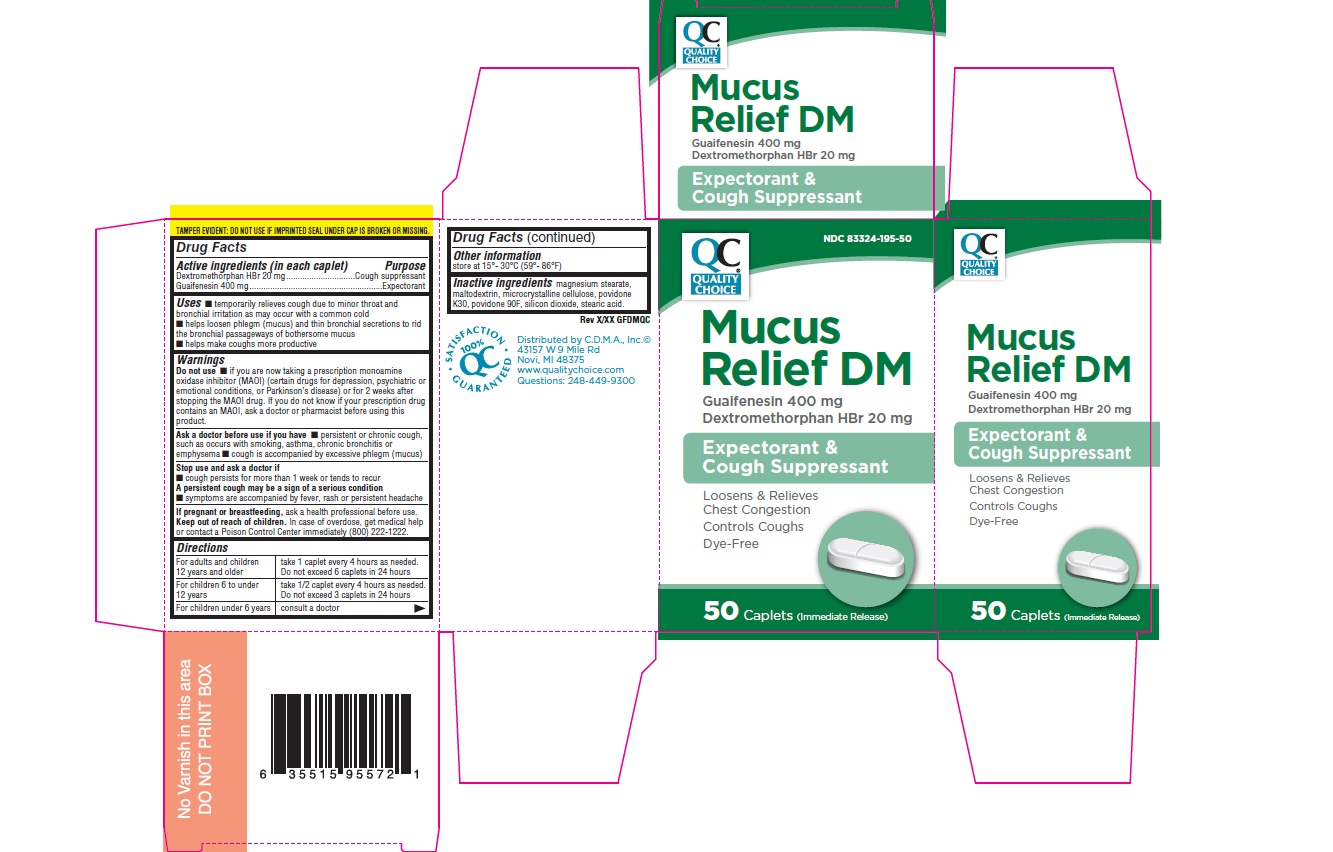 DRUG LABEL: Quality Choice Mucus Relief DM
NDC: 83324-195 | Form: TABLET
Manufacturer: Chain Drug Marketing Association
Category: otc | Type: HUMAN OTC DRUG LABEL
Date: 20260115

ACTIVE INGREDIENTS: DEXTROMETHORPHAN HYDROBROMIDE 20 mg/1 1; Guaifenesin 400 mg/1 1
INACTIVE INGREDIENTS: SILICON DIOXIDE; MAGNESIUM STEARATE; CELLULOSE, MICROCRYSTALLINE; MALTODEXTRIN; STEARIC ACID

DRUG FACTS

Active ingredient - (per tablet)
Dextromethorphan Hydrobromide 20mg
Guaifenesin 400mg

Purpose

Cough Suppressant

Expectorant

Uses

■ Temporarily relieves cough due to minor throat and bronchial irritation as may occur with a common cold
■ Helps loosen phlegm (mucus) and thin bronchial secretions to rid the bronchial passageways of bothersome mucus
■ Helps make coughs more productive.

Warnings

Do not use ■ if you are now taking a prescription monoamine oxidase (inhiMor~MAIO) (Certain drugs for depression, psychiatric or emotional conditioners or Parkinson's disease)or for 2 weeks after stopping MAIO drug, If you do not know if your prescription drug contains an MAIO, ask your doctor or pharmacist before using this product.

Ask doctor before use if you have
■ persistent or chronic cough, such as occurs with smoking, asthma, bronchitis or emphysma
■ cough is accompanied by excessive phlegm (mucus)

Stop use and ask doctor if
■ symptoms are accompanied by fever, rash or persistent headache
■ cough persists for more than 1 week or tends to recur.
A persistent cough may be a sign of a serious condition.

PREGNANCY OR BREAST FEEDING

If pregnant or breast-feeding, ask a health professional before use.

Keep out of reach of children. In case of overdose, get medical help or contact a Poison Center immediately.

Directions
■ Adults and children 12 years of age and over:take 1 tablet every 4 hours as needed.
■ Children 6 to 10 under 12 years of age: take 1/2 tablet every 4 hours as needed.
■ Children under 6 years of age: consult a doctor.
Do not exceed 6 doses in a 24 hour period or as directed by a doctor

Other Information

Store at 15°-30°C (59°-86°F)

INACTIVE INGREDIENT

Inactive Ingredients magnesium stearate, microcrystalline cellulose. May also contain (colloidal) silicon dioxide, (co) povidone, dicalcium phosphate, maltodextrin, sodium starch glycolate, stearic acid.